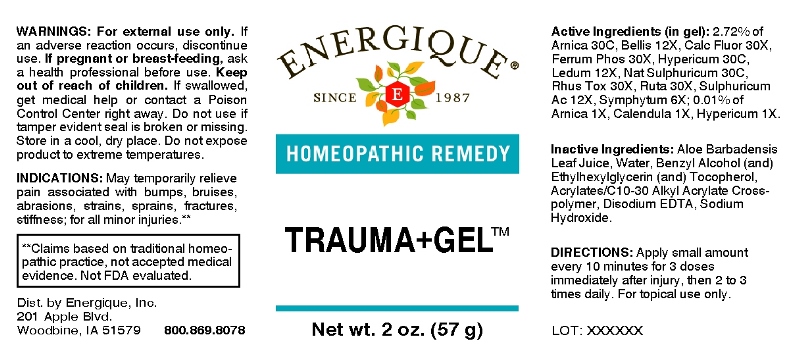 DRUG LABEL: Trauma plus Gel
NDC: 44911-0466 | Form: GEL
Manufacturer: Energique, Inc.
Category: homeopathic | Type: HUMAN OTC DRUG LABEL
Date: 20201002

ACTIVE INGREDIENTS: CALENDULA OFFICINALIS FLOWERING TOP 1 [hp_X]/1 g; ARNICA MONTANA 1 [hp_X]/1 g; HYPERICUM PERFORATUM 1 [hp_X]/1 g; COMFREY ROOT 6 [hp_X]/1 g; BELLIS PERENNIS 12 [hp_X]/1 g; LEDUM PALUSTRE TWIG 12 [hp_X]/1 g; SULFURIC ACID 12 [hp_X]/1 g; CALCIUM FLUORIDE 30 [hp_X]/1 g; FERROSOFERRIC PHOSPHATE 30 [hp_X]/1 g; TOXICODENDRON PUBESCENS LEAF 30 [hp_X]/1 g; RUTA GRAVEOLENS FLOWERING TOP 30 [hp_X]/1 g; SODIUM SULFATE 30 [hp_C]/1 g
INACTIVE INGREDIENTS: WATER; CARBOMER INTERPOLYMER TYPE A (ALLYL SUCROSE CROSSLINKED); BENZYL ALCOHOL; ETHYLHEXYLGLYCERIN; TOCOPHEROL; SODIUM HYDROXIDE; EDETATE DISODIUM

Drug Facts:

ACTIVE INGREDIENTS:

(in gel): 2.72% of Arnica Montana 30C, Bellis Perennis 12X, Calcarea Fluorica 30X, Ferrum Phosphoricum 30X, Hypericum Perforatum 30C, Ledum Palustre 12X, Natrum Sulphuricum 30C, Rhus Tox 30X, Ruta Graveolens 30X, Sulphuricum Acidum 12X, Symphytum Officinale 6X; 0.01% of Arnica Montana 1X, Calendula Officinalis 1X, Hypericum Perforatum 1X.

INDICATIONS:

May temporarily relieve pain associated with bumps, bruises, abrasions, strains, sprains, fractures, stiffness; for all minor injuries.**

**Claims based on traditional homeopathic practice, not accepted medical evidence. Not FDA evaluated.

WARNINGS:

For external use only. If an adverse reaction occurs, discontinue use.

If pregnant or breast-feeding, ask a health professional before use.

Keep out of reach of children. If swallowed, get medical help or contact a Poison Control Center right away.

Do not use if tamper evident seal is broken or missing.

Store in a cool, dry place. Do not expose product to extreme temperatures.

Keep out of reach of children. If swallowed, get medical help or contact a Poison Control Center right away.

DIRECTIONS:

Apply small amount every 10 minutes for 3 doses immediately after injury, then 2 to 3 times daily. For topical use only.

INDICATIONS:

May temporarily relieve pain associated with bumps, bruises, abrasions, strains, sprains, fractures, stiffness; for all minor injuries.**

**Claims based on traditional homeopathic practice, not accepted medical evidence. Not FDA evaluated.

INACTIVE INGREDIENTS:

Purified Water, Acrylates/C10-30 Alkyl Acrylate Crosspolymer, Benzyl Alcohol, Ethylhexylglycerin, Tocopherol, Sodium Hydroxide, Aloe Barbadensis 200X, Edetate Disodium (EDTA).

QUESTIONS:

Dist. by Energique, Inc.

201 Apple Blvd.

Woodbine, IA 51579 800.869.8078

PACKAGE LABEL DISPLAY:

ENERGIQUE

SINCE 1987

HOMEOPATHIC REMEDY

TRAUMA+GEL

Net wt. 2 oz. (57 g)